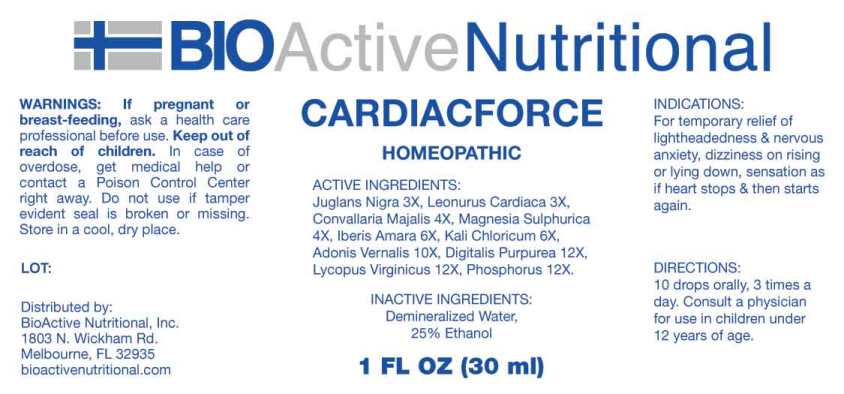 DRUG LABEL: Cardiacforce
NDC: 43857-0607 | Form: LIQUID
Manufacturer: BioActive Nutritional, Inc.
Category: homeopathic | Type: HUMAN OTC DRUG LABEL
Date: 20230608

ACTIVE INGREDIENTS: BLACK WALNUT 3 [hp_X]/1 mL; LEONURUS CARDIACA WHOLE 3 [hp_X]/1 mL; CONVALLARIA MAJALIS 4 [hp_X]/1 mL; MAGNESIUM SULFATE HEPTAHYDRATE 4 [hp_X]/1 mL; IBERIS AMARA SEED 6 [hp_X]/1 mL; POTASSIUM CHLORATE 6 [hp_X]/1 mL; ADONIS VERNALIS WHOLE 10 [hp_X]/1 mL; DIGITALIS 12 [hp_X]/1 mL; LYCOPUS VIRGINICUS WHOLE 12 [hp_X]/1 mL; PHOSPHORUS 12 [hp_X]/1 mL
INACTIVE INGREDIENTS: WATER; ALCOHOL

DRUG FACTS:

ACTIVE INGREDIENTS:

Juglans Nigra 3X, Leonurus Cardiaca 3X, Convallaria Majalis 4X, Magnesia Sulphurica 4X, Iberis Amara 6X, Kali Chloricum 6X, Adonis Vernalis 10X, Digitalis Purpurea 12X, Lycopus Virginicus 12X, Phosphorus 12X.

INDICATIONS:

For temporary relief of lightheadedness & nervous anxiety, dizziness on rising or lying down, sensation as if heart stops & then starts again.

WARNINGS:

If pregnant or breast-feeding, ask a health care professional before use.

Keep out of reach of children. In case of overdose, get medical help or contact a Poison Control Center right away.

Do not use if tamper evident seal is broken or missing.

Store in cool, dry place.

Keep out of reach of children. In case of overdose, get medical help or contact a Poison Control Center right away.

DIRECTIONS:

10 drops orally, 3 times a day. Consult a physician for use in children under 12 years of age.

INDICATIONS:

For temporary relief of lightheadedness & nervous anxiety, dizziness on rising or lying down, sensation as if heart stops & then starts again.

INACTIVE INGREDIENTS:

Demineralized Water, 25% Ethanol

QUESTIONS:

Distributed by:

BioActive Nutritional, Inc.

1803 N. Wickham Rd.

Melbourne, FL 32935

bioactivenutritional.com

PACKAGE LABEL DISPLAY:

BIOActive Nutritional

CARDIACFORCE

HOMEOPATHIC

1 FL OZ (30 ml)